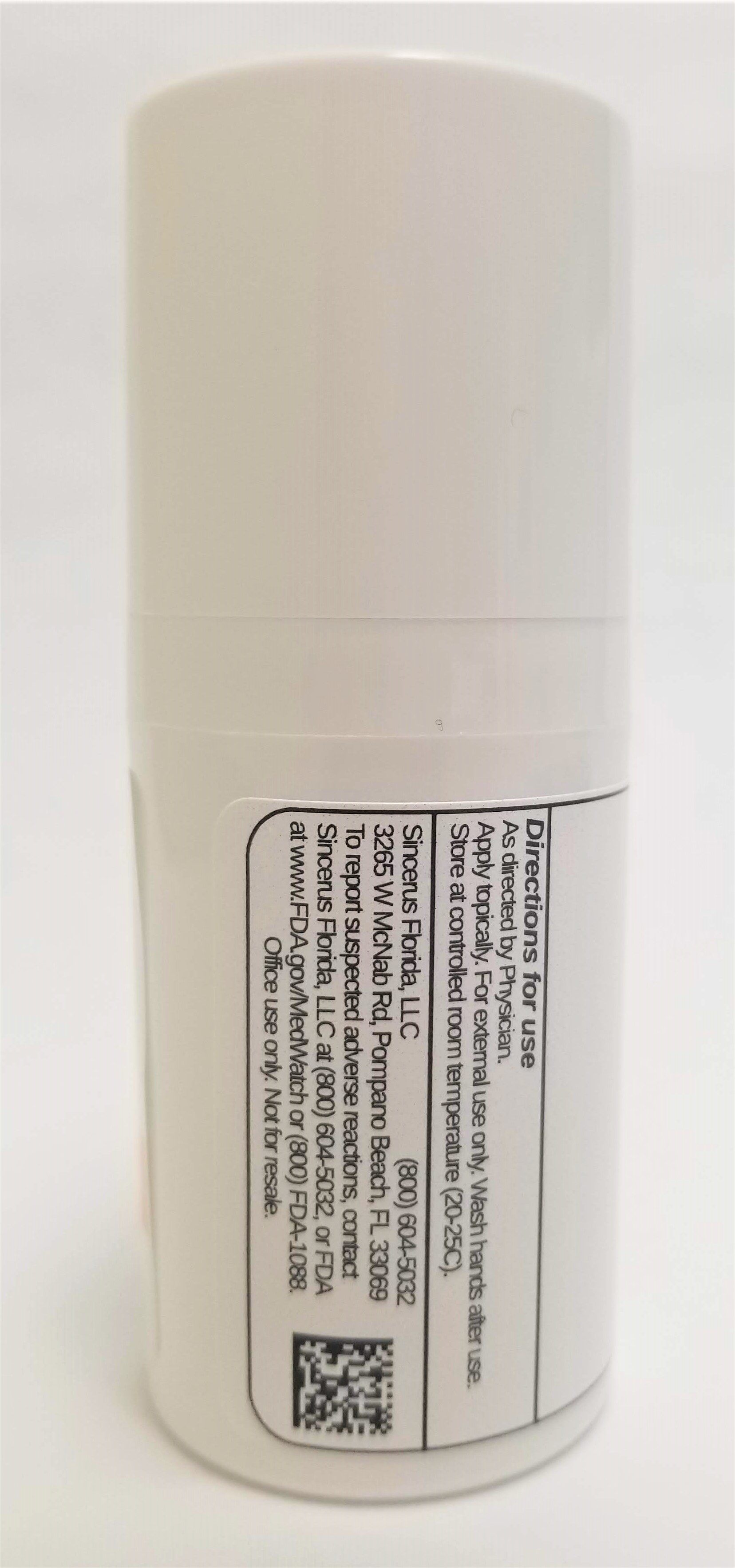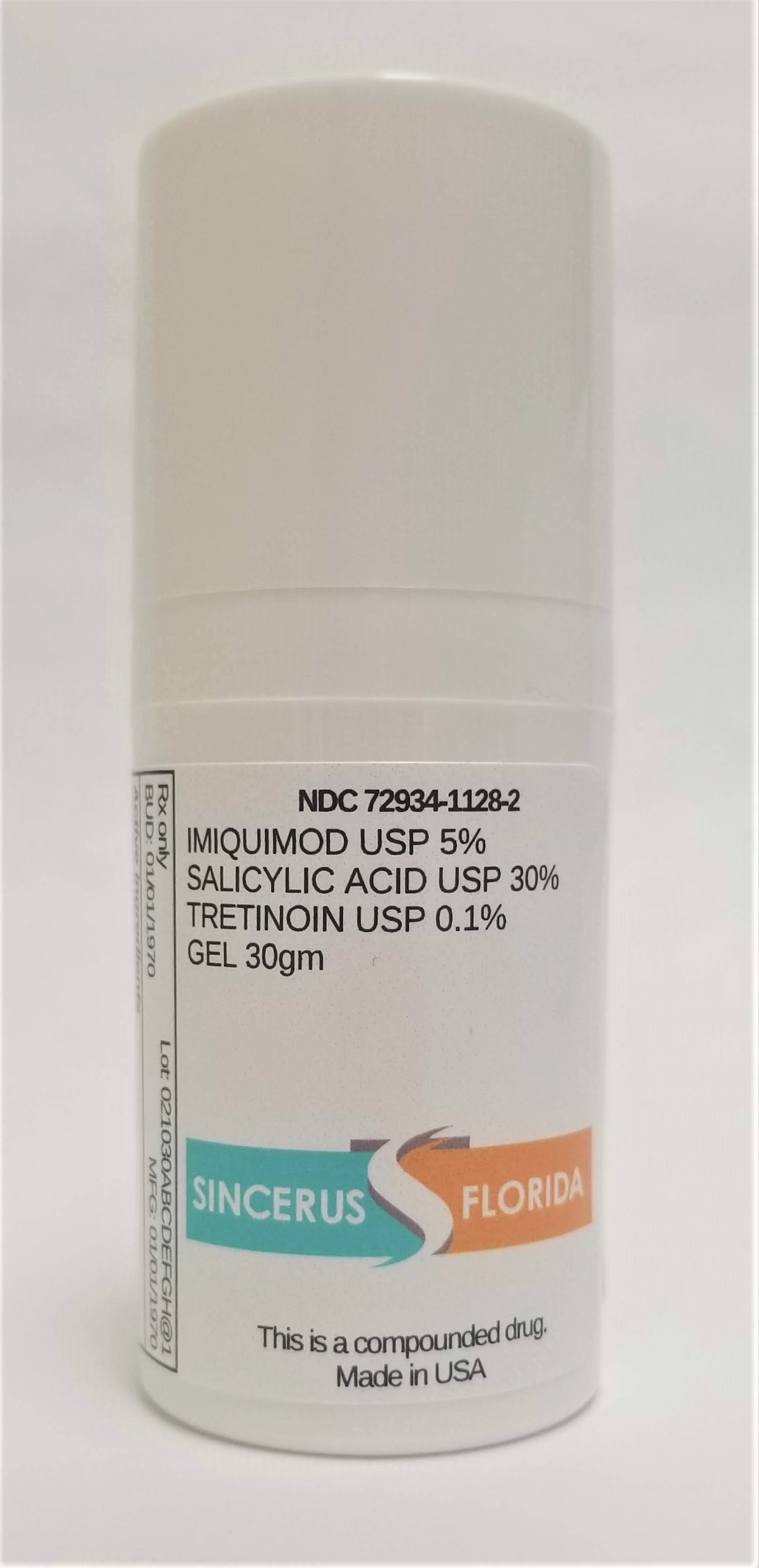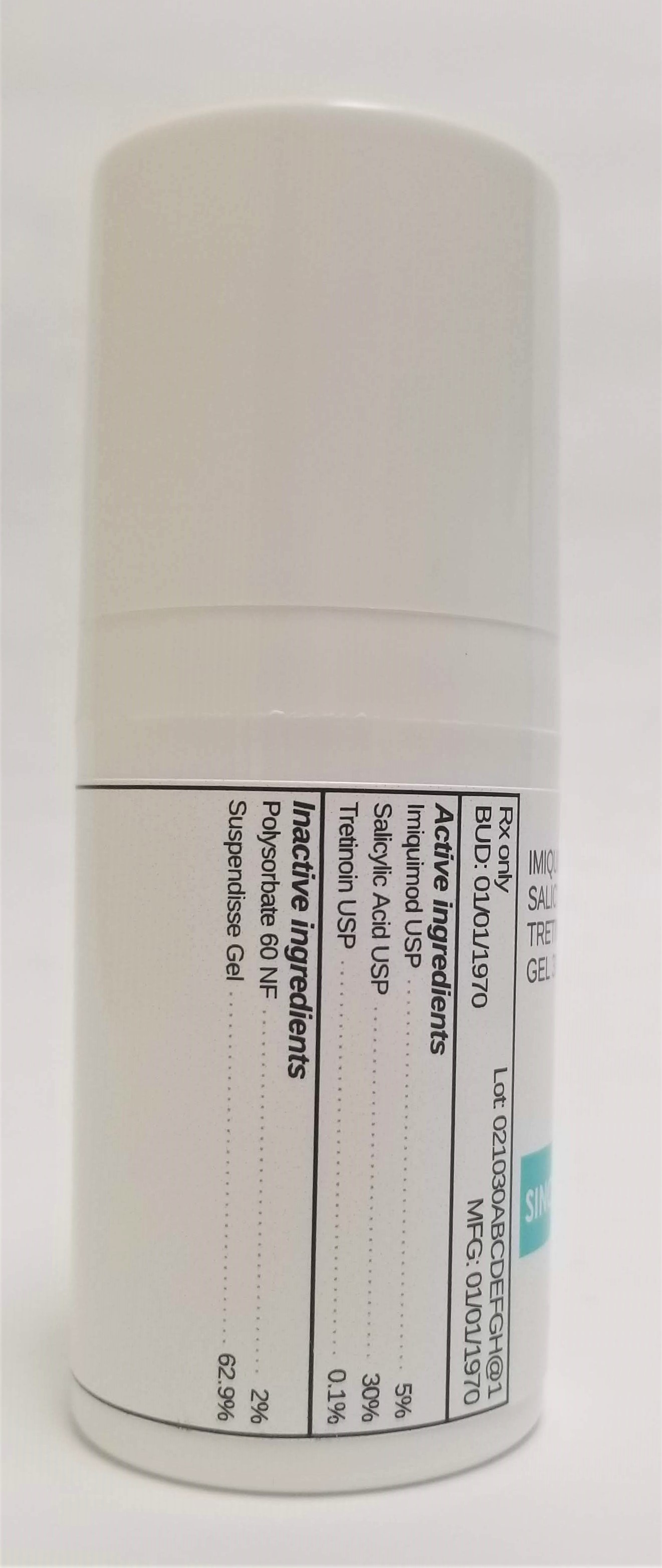 DRUG LABEL: IMIQUIMOD 5% / SALICYLIC ACID 30% / TRETINOIN 0.1%
NDC: 72934-1128 | Form: GEL
Manufacturer: Sincerus Florida, LLC
Category: prescription | Type: HUMAN PRESCRIPTION DRUG LABEL
Date: 20190506

ACTIVE INGREDIENTS: SALICYLIC ACID 30 g/100 g; TRETINOIN 0.1 g/100 g; IMIQUIMOD 5 g/100 g

IMIQUIMOD 5% / SALICYLIC ACID 30% / TRETINOIN 0.1%